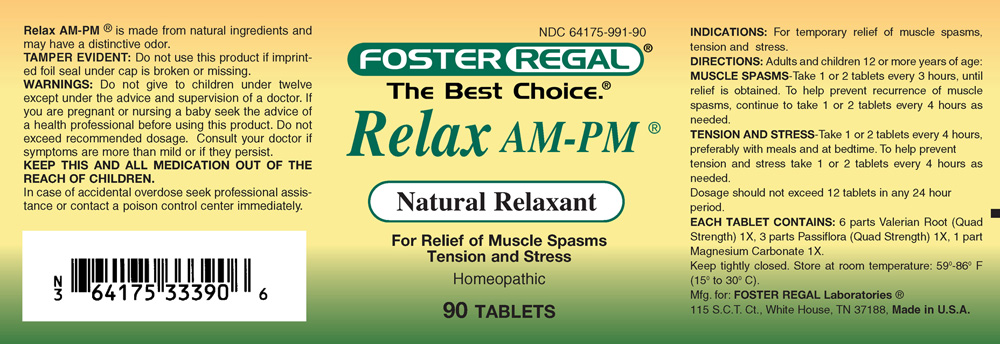 DRUG LABEL: Relax AM-PM
NDC: 64175-991 | Form: TABLET
Manufacturer: Foster Regal Laboratories
Category: homeopathic | Type: HUMAN OTC DRUG LABEL
Date: 20250106

ACTIVE INGREDIENTS: VALERIAN 6 [hp_X]/1 1; PASSIFLORA INCARNATA FLOWER 3 [hp_X]/1 1; MAGNESIUM CARBONATE 1 [hp_X]/1 1
INACTIVE INGREDIENTS: MALTODEXTRIN; SODIUM STARCH GLYCOLATE TYPE A POTATO; STEARIC ACID; SILICON DIOXIDE; LACTOSE MONOHYDRATE

Relax AM-PM

ACTIVE INGREDIENT

EACH TABLET CONTAINS:
6 parts Valerian Root (Quad-Strength) 1X, 3 parts Passiflora (Quad-Strength) 1X, 1 part Magnesium Carbonate 1X.

PURPOSE

For Relief of Muscle Spasms
Tension and Stress

KEEP OUT OF REACH OF CHILDREN

KEEP THIS AND ALL MEDICATION OUT OF THE REACH OF CHILDREN. In case of accidental overdose seek professional assistance or contact a poison control center immediately.

INDICATIONS AND USAGE

INDICATIONS: For temporary relief of muscle spasms, tension and stress.

WARNINGS

Warning: Do not give to children under twelve except under the advice and supervision of a doctor. If you are pregnant or nursing a baby seek the advice of a health professional before using this product. Do not exceed recommended dosage. Consult a doctor if symptoms are more than mild or if they persist.

DOSAGE AND ADMINISTRATION

Directions: Adults and children 12 or more years of age.

Muscle Spasms - Take 1 or 2 tablets every 3 hours, until relief is obtained. To help prevent recurrence of muscle spasms, continue to take 1 or 2 tablets every 4 hours as needed.

Tension and Stress - Take 1 or 2 tablets every 4 hours, preferably with meals and at bedtime. To help prevent tension and stress take 1 or 2 tablets every 4 hours as needed.

Dosage should not exceed 12 tablets in any 24 hour period.

INACTIVE INGREDIENT

Lactose Monohydrate, Maltodextrin, Sodium Starch Glycolate Type A Potato, Stearic Acid, Silica